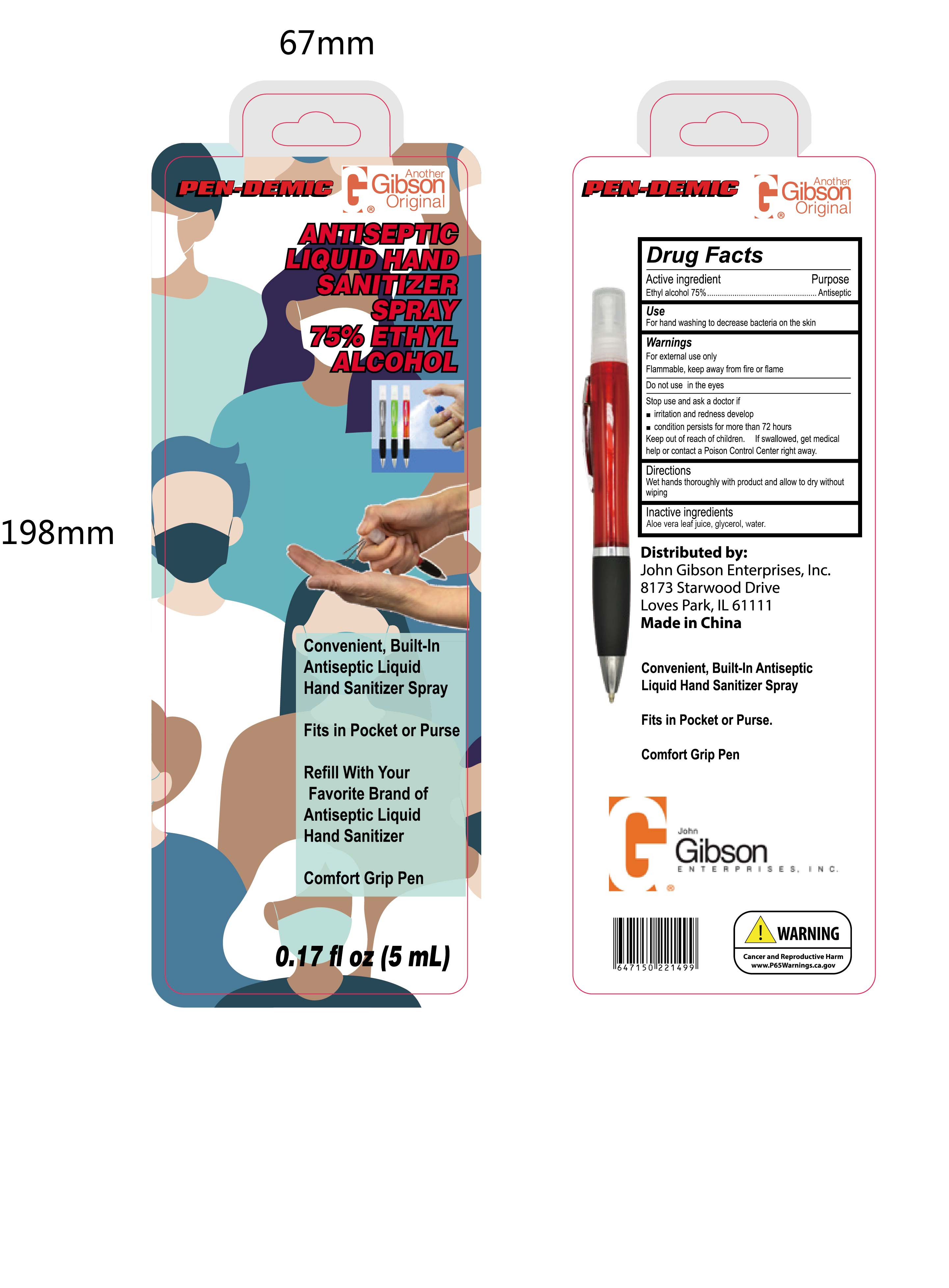 DRUG LABEL: 5ml hand sanitizer
NDC: 75273-007 | Form: SPRAY
Manufacturer: YIWU BAOLINA COSMETIC CO., LTD
Category: otc | Type: HUMAN OTC DRUG LABEL
Date: 20201220

ACTIVE INGREDIENTS: ALCOHOL 75 mL/100 mL
INACTIVE INGREDIENTS: GLYCERIN; ALOE VERA LEAF; WATER

75273-007
5ml hand sanitizer spray

Active Ingredient(s)

Ethyl alcohol 75%

Purpose

Antiseptic

Use

For handwashing to decrease bacteria on the skin

Warnings

For external use only
Flammable， keep away from fire or flame

Do not use in the eyes
Stop use and ask a doctor if
irritation and redness develop
condition persists for more than 72 hours

Keep out of reach of children.If swallowed， get medical help or contact a Poison Control Center right away.

Stop use and ask a doctor if
irritation and redness develop
condition persists for more than 72 hours

Keep out of reach of children.If swallowed， get medical help or contact a Poison Control Center right away.

Directions

Wet hands thoroughly with product and allow to dry wthout wiping

Other information

- Store between 15-30C (59-86F)
- Avoid freezing and excessive heat above 40C (104F)

Inactive ingredients

Aloe vera leaf juice， glycerol, water.

Package Label - Principal Display Panel

75273-007-01 5ml hand sanitizer spray